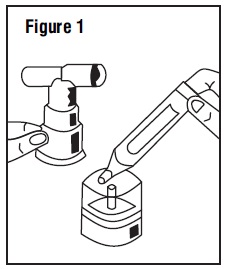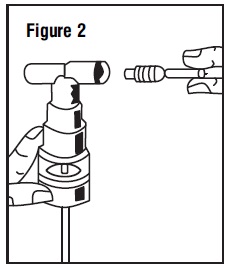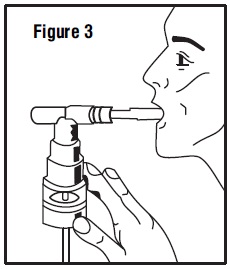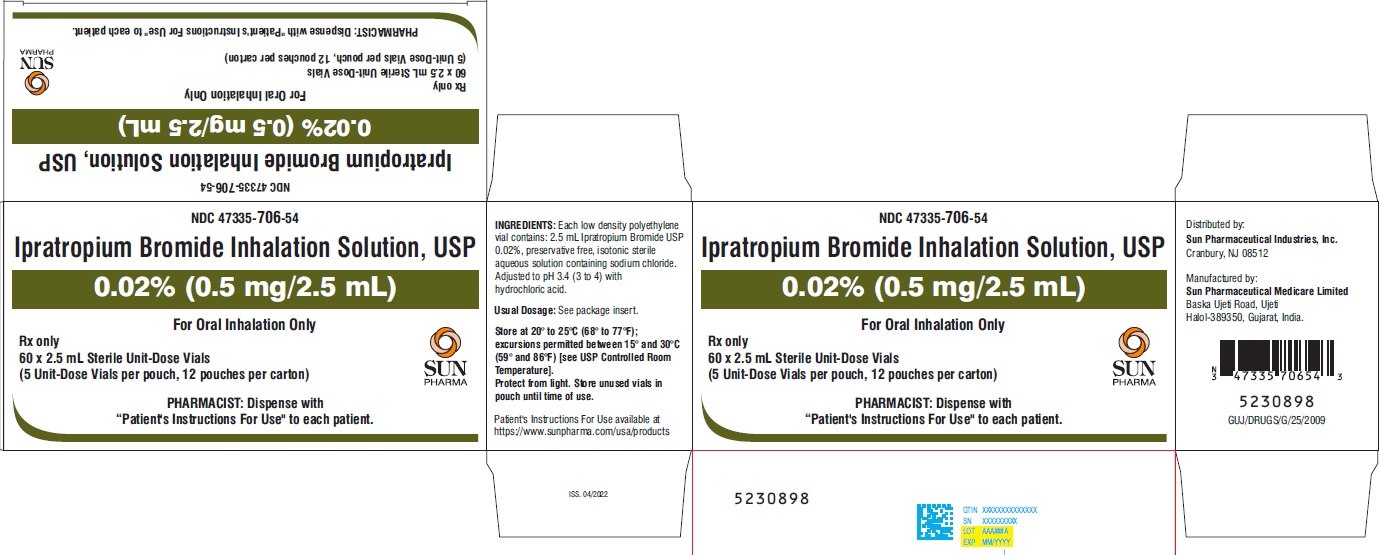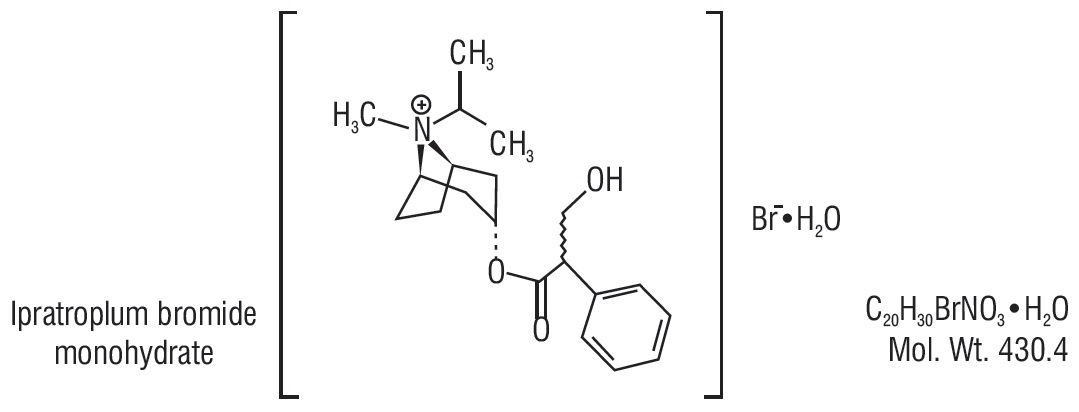 DRUG LABEL: Ipratropium Bromide
NDC: 47335-706 | Form: SOLUTION
Manufacturer: Sun Pharmaceutical Industries, Inc.
Category: prescription | Type: Human Prescription Drug Label
Date: 20220413

ACTIVE INGREDIENTS: IPRATROPIUM BROMIDE 0.5 mg/2.5 mL
INACTIVE INGREDIENTS: HYDROCHLORIC ACID; SODIUM CHLORIDE; WATER

Ipratropium Bromide Inhalation Solution, USP 0.02%
Rx only
PRESCRIBING INFORMATION
FOR INHALATION USE ONLY–NOT FOR INJECTION.

DESCRIPTION

The active ingredient in Ipratropium Bromide Inhalation Solution, USP is ipratropium bromide monohydrate, USP. It is an anticholinergic bronchodilator chemically described as 8-azoniabicyclo[3.2.1]-octane,3-(3-hydroxy-1-oxo-2-phenylpropoxy)-8-methyl-8-(1- methylethyl)-, bromide, monohydrate (endo, syn)-,(±)-; a synthetic quaternary ammonium compound, chemically related to atropine.
Ipratropium bromide is a white crystalline substance, freely soluble in water and lower alcohols. It is a quaternary ammonium compound and thus exists in an ionized state in aqueous solutions. It is relatively insoluble in non-polar media.
Ipratropium Bromide Inhalation Solution, USP is administered by oral inhalation with the aid of a nebulizer. Each mL contains ipratropium bromide, USP 0.02% (anhydrous basis) in a sterile, preservative-free, isotonic saline solution, pH adjusted to 3.4 (3 to 4) with hydrochloric acid.

CLINICAL PHARMACOLOGY

Ipratropium Bromide Inhalation Solution is an anticholinergic (parasympatholytic) agent that, based on animal studies, appears to inhibit vagally-mediated reflexes by antagonizing the action of acetylcholine, the transmitter agent released from the vagus nerve.
Anticholinergics prevent the increases in intracellular concentration of cyclic guanosine monophosphate (cyclic GMP) which are caused by interaction of acetylcholine with the muscarinic receptor on bronchial smooth muscle.
The bronchodilation following inhalation of Ipratropium Bromide Inhalation Solution is primarily a local, site-specific effect, not a systemic one. Much of an administered dose is swallowed but not absorbed as shown by fecal excretion studies. Following nebulization of a 2 mg dose, a mean 7% of the dose was absorbed into the systemic circulation either from the surface of the lung or from the gastrointestinal tract. The half-life of elimination is about 1.6 hours after intravenous administration. Ipratropium bromide is minimally (0 to 9% in vitro) bound to plasma albumin and α1–acid glycoproteins. It is partially metabolized. Autoradiographic studies in rats have shown that ipratropium bromide does not penetrate the blood-brain barrier. Ipratropium Bromide Inhalation Solution has not been studied in patients with hepatic or renal insufficiency. It should be used with caution in those patient populations.
In controlled twelve-week studies in patients with bronchospasm associated with chronic obstructive pulmonary disease (chronic bronchitis and emphysema) significant improvements in pulmonary function (FEV1 increases of 15% or more) occurred within 15 to 30 minutes, reached a peak in 1 to 2 hours and persisted for periods of 4 to 5 hours in the majority of patients, with about 25 to 38% of the patients demonstrating increases of 15% or more for at least 7 to 8 hours. Continued effectiveness of ipratropium bromide was demonstrated throughout the 12-week period. In addition, significant increases in forced vital capacity (FVC) have been demonstrated. However, ipratropium bromide did not consistently produce significant improvement in subjective symptom scores nor in quality of life scores over the 12-week duration of study.
Additional controlled 12-week studies were conducted to evaluate the safety and effectiveness of Ipratropium Bromide Inhalation Solution administered concomitantly with the beta adrenergic bronchodilator solutions metaproterenol and albuterol compared with the administration of each of the beta agonists alone. Combined therapy produced significant additional improvement in FEV1 and FVC. On combined therapy, the median duration of 15% improvement in FEV1 was 5 to 7 hours, compared with 3 to 4 hours in patients receiving a beta agonist alone.

INDICATIONS AND USAGE

Ipratropium Bromide Inhalation Solution administered either alone or with other bronchodilators, especially beta adrenergics, is indicated as a bronchodilator for maintenance treatment of bronchospasm associated with chronic obstructive pulmonary disease, including chronic bronchitis and emphysema.

CONTRAINDICATIONS

Ipratropium bromide is contraindicated in known or suspected cases of hypersensitivity to ipratropium bromide, or to atropine and its derivatives.

WARNINGS

The use of Ipratropium Bromide Inhalation Solution as a single agent for the relief of bronchospasm in acute COPD exacerbation has not been adequately studied. Drugs with faster onset of action may be preferable as initial therapy in this situation. Combination of Ipratropium Bromide Inhalation Solution and beta agonists has not been shown to be more effective than either drug alone in reversing the bronchospasm associated with acute COPD exacerbation.
Immediate hypersensitivity reactions may occur after administration of ipratropium bromide, as demonstrated by rare cases of urticaria, angioedema, rash, bronchospasm and oropharyngeal edema.

PRECAUTIONS

General

Ipratropium bromide should be used with caution in patients with narrow angle glaucoma, prostatic hypertrophy or bladder neck obstruction.

Information for Patients

Patients should be advised that mydriasis, temporary blurring of vision, precipitation or worsening of narrow-angle glaucoma or eye pain may result if the solution comes into direct contact with the eyes. Use of a nebulizer with mouthpiece rather than face mask may be preferable, to reduce the likelihood of the nebulizer solution reaching the eyes. Patients should be advised that Ipratropium Bromide Inhalation Solution can be mixed in the nebulizer with albuterol or metaproterenol if used within one hour. Drug stability and safety of Ipratropium Bromide inhalation solution when mixed with other drugs in a nebulizer have not been established. Patients should be reminded that Ipratropium Bromide Inhalation Solution should be used consistently as prescribed throughout the course of therapy.

Drug Interactions

Ipratropium bromide has been shown to be a safe and effective bronchodilator when used in conjunction with beta adrenergic bronchodilators. Ipratropium bromide has also been used with other pulmonary medications, including methylxanthines and corticosteroids, without adverse drug interactions.

Carcinogenesis, Mutagenesis, Impairment of Fertility

Two-year oral carcinogenicity studies in rats and mice have revealed no carcinogenic potential at dietary doses up to 6 mg/kg/day of ipratropium bromide.
Results of various mutagenicity studies (Ames test, mouse dominal lethal test, mouse micronucleus test and chromosome aberration of bone marrow in Chinese hamsters) were negative.
Fertility of male or female rats at oral doses up to 50 mg/kg/day was unaffected by ipratropium bromide administration. At doses above 90 mg/kg, increased resorption and decreased conception rates were observed.

Pregnancy

Teratogenic Effects

Oral reproduction studies performed in mice, rats and rabbits at doses of 10, 100, and 125 mg/kg respectively and inhalation reproduction studies in rats and rabbits at doses of 1.5 and 1.8 mg/kg (or approximately 38 and 45 times the recommended human daily dose) respectively, have demonstrated no evidence of teratogenic effects as a result of ipratropium bromide. However, no adequate or well controlled studies have been conducted in pregnant women. Because animal reproduction studies are not always predictive of human response, ipratropium bromide should be used during pregnancy only if clearly needed.

Nursing Mothers

It is not known whether ipratropium bromide is excreted in human milk. Although lipid-insoluble quaternary bases pass into breast milk, it is unlikely that ipratropium bromide would reach the infant to a significant extent, especially when taken by inhalation since ipratropium bromide is not well absorbed systemically after inhalation or oral administration. However, because many drugs are excreted in human milk, caution should be exercised when ipratropium bromide is administered to a nursing woman.

Pediatric Use

Safety and effectiveness in pediatric patients below the age of 12 have not been established.

ADVERSE REACTIONS

Adverse reaction information concerning Ipratropium Bromide Inhalation Solution is derived from 12-week active-controlled clinical trials. Additional information is derived from foreign postmarketing experience and the published literature.
All adverse events, regardless of drug relationship, reported by three percent or more patients in the 12-week controlled clinical trials appear in the table.
Additional adverse reactions reported in less than three percent of the patients treated with ipratropium bromide include tachycardia, palpitations, eye pain, urinary retention, urinary tract infection and urticaria. Cases of precipitation or worsening of narrow-angle glaucoma, mydriasis, and acute eye pain have been reported.
Lower respiratory adverse reactions (bronchitis, dyspnea and bronchospasm) were the most common events leading to discontinuation of ipratropium bromide therapy in the 12-week trials. Headache, mouth dryness and aggravation of COPD symptoms are more common when the total daily dose of ipratropium bromide equals or exceeds 2,000 mcg. Allergic-type reactions such as skin rash, angioedema of tongue, lips and face, urticaria, laryngospasm and anaphylactic reaction have been reported. Many of the patients had a history of allergies to other drugs and/or foods.

All Adverse Events, From a Double-blind, Parallel, 12-week Study of Patients with COPD [All adverse events, regardless of drug relationship, reported by the three percent or more patients in the 12-week controlled clinical trials.]
 | PERCENT OF PATIENTS
 | Ipratropium Bromide (500 mcg t.i.d.) n = 219 | Metaproterenol (15 mg t.i.d.) n = 212 | Ipratropium Bromide/ Metaproterenol (500 mcg t.i.d./15 mg t.i.d.) n = 108 | Albuterol (2.5 mg t.i.d.) n = 205 | Ipratropium Bromide/ Albuterol (500 mcg t.i.d./2.5 mg t.i.d.) n = 100
Body as a Whole-General Disorders
Headache | 6.4 | 5.2 | 6.5 | 6.3 | 9
Pain | 4.1 | 3.3 | 0.9 | 2.9 | 5
Influenza-like symptoms | 3.7 | 4.7 | 6.5 | 0.5 | 1
Back Pain | 3.2 | 1.9 | 1.9 | 2.4 | 0
Chest Pain | 3.2 | 4.2 | 5.6 | 2 | 1
Cardiovascular Disorders
Hypertension/hypertension Aggravated | 0.9 | 1.9 | 0.9 | 1.5 | 4
Central & Peripheral Nervous System
Dizziness | 2.3 | 3.3 | 1.9 | 3.9 | 4
Insomnia | 0.9 | 0.5 | 4.6 | 1 | 1
Tremor | 0.9 | 7.1 | 8.3 | 1 | 0
Nervousness | 0.5 | 4.7 | 6.5 | 1 | 1
Gastrointestinal System Disorders
Mouth Dryness | 3.2 | 0 | 1.9 | 2 | 3
Nausea | 4.1 | 3.8 | 1.9 | 2.9 | 2
Constipation | 0.9 | 0 | 3.7 | 1 | 1
Musculo-skeletal System Disorders
Arthritis | 0.9 | 1.4 | 0.9 | 0.5 | 3
Respiratory System Disorders (Lower)
Coughing | 4.6 | 8 | 6.5 | 5.4 | 6
Dyspnea | 9.6 | 13.2 | 16.7 | 12.7 | 9
Bronchitis | 14.6 | 24.5 | 15.7 | 16.6 | 20
Bronchospasm | 2.3 | 2.8 | 4.6 | 5.4 | 5
Sputum Increased | 1.4 | 1.4 | 4.6 | 3.4 | 0
Respiratory Disorder | 0 | 6.1 | 6.5 | 2 | 4
Respiratory System Disorders (Upper)
Upper Respiratory Tract Infection | 13.2 | 11.3 | 9.3 | 12.2 | 16
Pharyngitis | 3.7 | 4.2 | 5.6 | 2.9 | 4
Rhinitis | 2.3 | 4.2 | 1.9 | 2.4 | 0
Sinusitis | 2.3 | 2.8 | 0.9 | 5.4 | 4

OVERDOSAGE

Acute systemic overdosage by inhalation is unlikely since ipratropium bromide is not well absorbed after inhalation at up to four-fold the recommended dose, or after oral administration at up to forty-fold the recommended dose. The oral LD50 of ipratropium bromide ranged between 1,001 and 2,010 mg/kg in mice; between 1,667 and 4,000 mg/kg in rats; and between 400 and 1,300 mg/kg in dogs.

DOSAGE AND ADMINISTRATION

The usual dosage of Ipratropium Bromide Inhalation Solution is 500 mcg (1 Unit-Dose Vial) administered three to four times a day by oral nebulization, with doses 6 to 8 hours apart. Ipratropium Bromide Inhalation Solution Unit-Dose Vials contain 500 mcg ipratropium bromide, USP anhydrous in 2.5 mL normal saline. Ipratropium Bromide Inhalation Solution can be mixed in the nebulizer with albuterol or metaproterenol if used within one hour. Drug stability and safety of Ipratropium Bromide Inhalation Solution when mixed with other drugs in a nebulizer have not been established.

HOW SUPPLIED

Ipratropium Bromide Inhalation Solution, USP is a clear, colorless solution supplied in a unit-dose vial containing 2.5 mL. Supplied in cartons as listed below:
NDC 47335-706-49 carton of 25 vials (5 vials per foil pouch)

NDC 47335-706-52 carton of 30 vials (5 vials per foil pouch)

NDC 47335-706-54 carton of 60 vials (5 vials per foil pouch)
Each vial is made from a low density polyethylene (LDPE) resin.
Store at 20° to 25°C (68° to 77°F); excursions permitted between 15° and 30°C (59° and 86°F) [see USP Controlled Room Temperature]. Protect from light. Store in pouch until time of use.
Dispense with Patient's Instructions For Use available at: https://www.sunpharma.com/usa/products

Patient's Instructions for Use

Ipratropium Bromide (IH-pruh-TROE-pee-uhm BROE-mide)
Inhalation Solution, USP 0.02%

Read complete instructions carefully before using.

1. Remove vial from the foil pouch.

2. Twist open the top of one unit dose vial and squeeze the contents into the nebulizer reservoir (Figure 1).

3. Connect the nebulizer reservoir to the mouthpiece or face mask (Figure 2).
4. Connect the nebulizer to the compressor.

5. Sit in a comfortable, upright position; place the mouthpiece in your mouth (Figure 3) or put on the face mask and turn on the compressor. If a face mask is used, care should be taken to avoid leakage around the mask as temporary blurring of vision, pupil enlargement, precipitation or worsening of narrow-angle glaucoma, or eye pain may occur if the solution comes into direct contact with the eyes.

6. Breathe as calmly, deeply, and evenly as possible until no more mist is formed in the nebulizer chamber (about 5 to 15 minutes). At this point, the treatment is finished.

7. Clean the nebulizer (see manufacturer’s instructions).

Note: Use only as directed by your physician. More frequent administration or higher doses are not recommended. Ipratropium Bromide Inhalation Solution can be mixed in the nebulizer with albuterol or metaproterenol if used within one hour but not with other drugs. Drug stability and safety of Ipratropium Bromide Inhalation Solution when mixed with other drugs in a nebulizer have not been established.

Store at 20° to 25°C (68° to 77°F); excursions permitted between 15° and 30°C (59° and 86°F) [see USP Controlled Room Temperature]. Protect from light. Store in pouch until time of use.

ADDITIONAL INSTRUCTIONS: __________________________________________

Dispense with Patient's Instructions For Use available at: https://www.sunpharma.com/usa/products
Distributed by:
Sun Pharmaceutical Industries, Inc.
Cranbury, NJ 08512

Manufactured by:

Sun Pharmaceutical Medicare Limited

Baska Ujeti Road, Ujeti

Halol-389350, Gujarat, India

5230899

ISS. 4/2022

PACKAGE LABEL.PRINCIPAL DISPLAY PANEL

NDC 47335-706-54
Ipratropium Bromide Inhalation Solution, USP
0.02% (0.5 mg/2.5 mL)
For Oral Inhalation Only
Rx only
60 X 2.5 mL Sterile Unit-Dose Vials
(5 Unit-Dose Vials per pouch, 12 pouches per carton)
PHARMACIST: Dispense with "Patient's Instructions For Use" to each patient.
SUN PHARMA